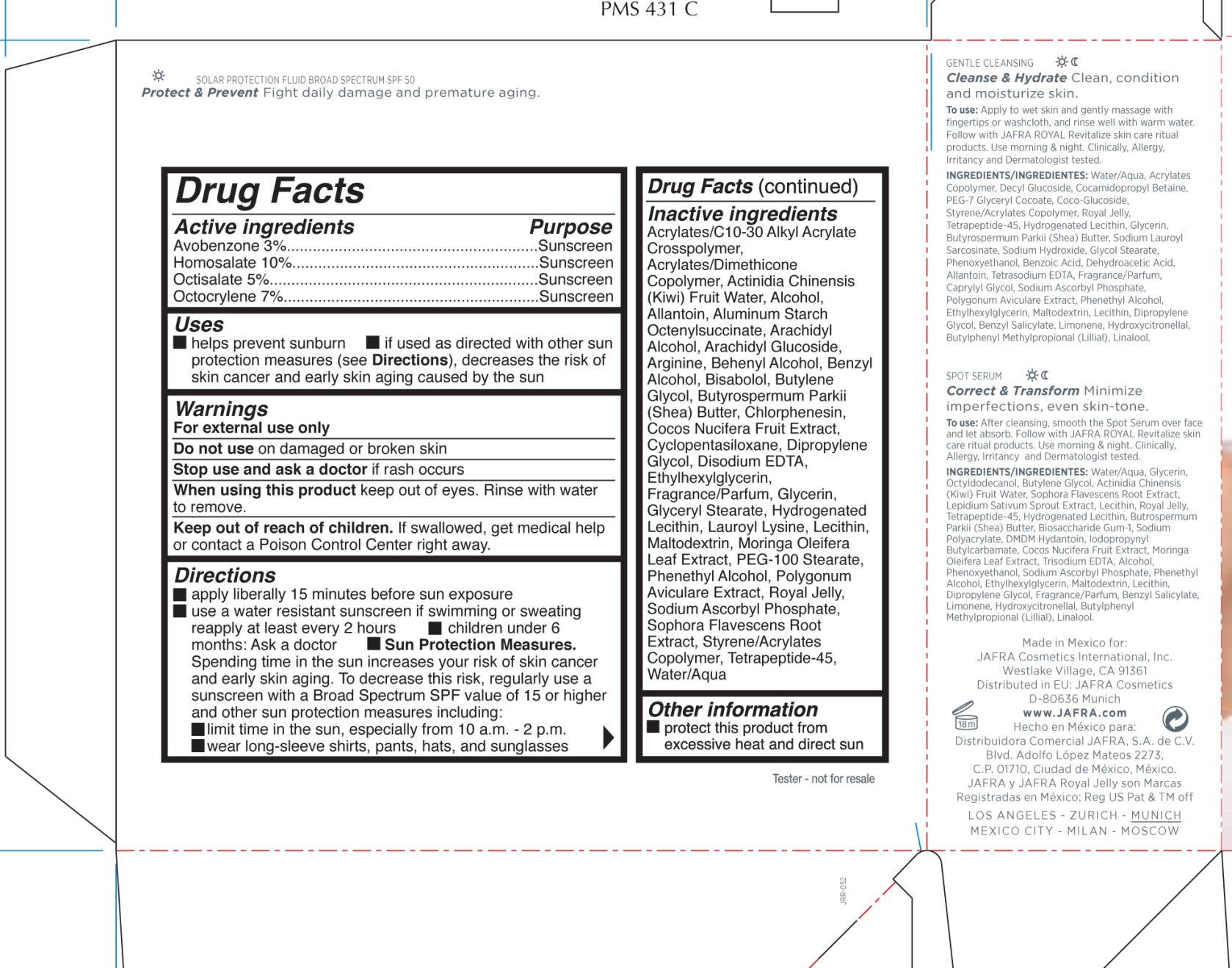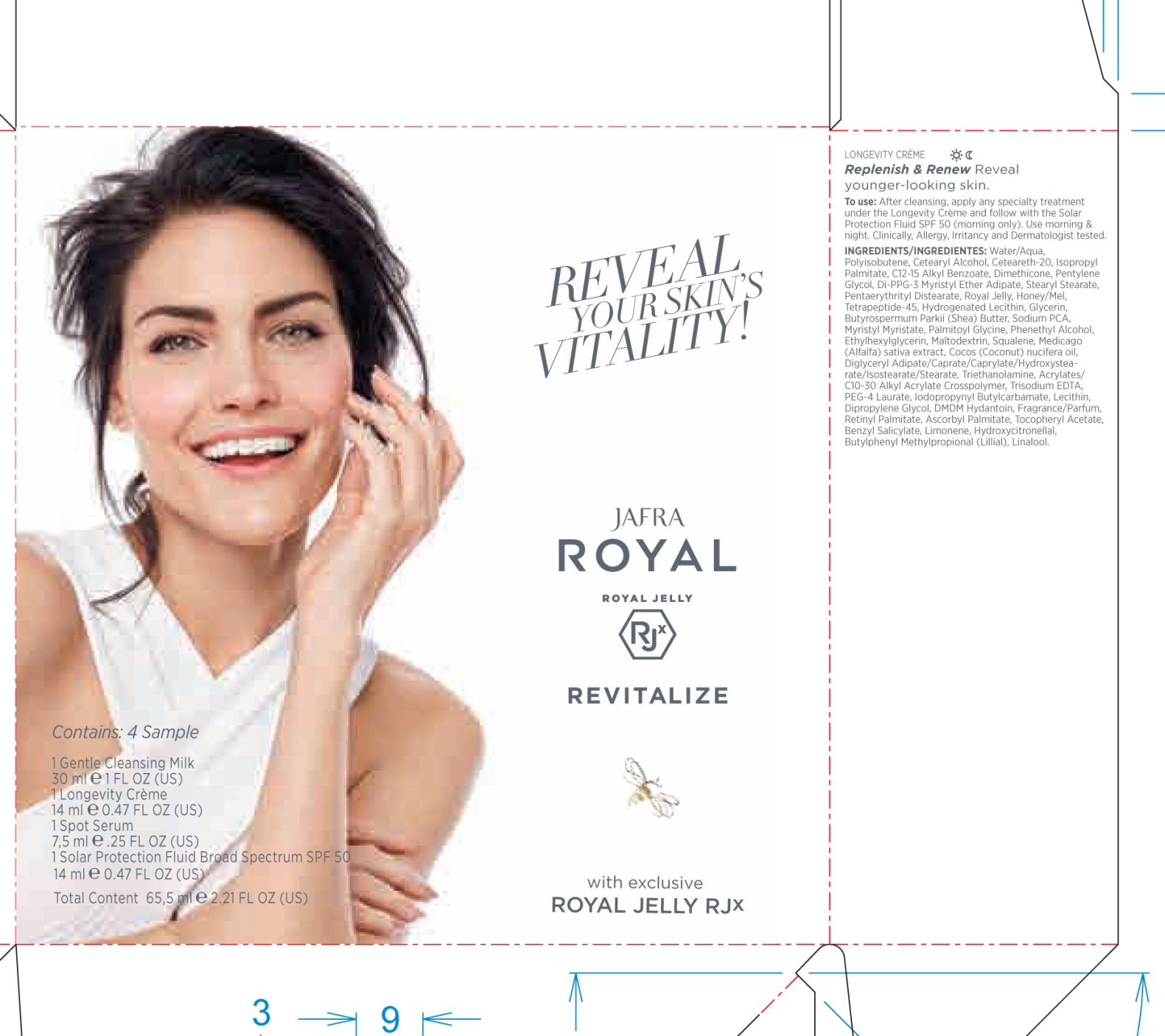 DRUG LABEL: Jafra Royal Jelly Revitalize
NDC: 68828-500 | Form: KIT | Route: TOPICAL
Manufacturer: JAFRA COSMETICS INTERNATIONAL
Category: otc | Type: HUMAN OTC DRUG LABEL
Date: 20180420

ACTIVE INGREDIENTS: AVOBENZONE 3 g/100 mL; HOMOSALATE 10 g/100 mL; OCTISALATE 5 g/100 mL; OCTOCRYLENE 7 g/100 mL
INACTIVE INGREDIENTS: CARBOMER COPOLYMER TYPE A (ALLYL PENTAERYTHRITOL CROSSLINKED); KIWI FRUIT OIL; ALCOHOL; ALLANTOIN; ALUMINUM STARCH OCTENYLSUCCINATE; ARACHIDYL ALCOHOL; ARACHIDYL GLUCOSIDE; ARGININE; DOCOSANOL; BENZYL ALCOHOL; LEVOMENOL; BUTYLENE GLYCOL; SHEA BUTTER; CHLORPHENESIN; COCONUT; CYCLOMETHICONE 5; DIPROPYLENE GLYCOL; EDETATE DISODIUM; ETHYLHEXYLGLYCERIN; GLYCERIN; GLYCERYL MONOSTEARATE; HYDROGENATED SOYBEAN LECITHIN; LAUROYL LYSINE; LECITHIN, SOYBEAN; MALTODEXTRIN; MORINGA OLEIFERA LEAF; PEG-100 STEARATE; PHENYLETHYL ALCOHOL; POLYGONUM AVICULARE TOP; ROYAL JELLY; SODIUM ASCORBYL PHOSPHATE; SOPHORA FLAVESCENS ROOT; WATER

Jafra Royal Jelly Revitalize
Solar Protection Fluid Broad Spectrum SPF 50

Active ingredients Purpose
Avobenzone 3%..........................................................Sunscreen
Homosalate 10%.........................................................Sunscreen
Octisalate 5%..............................................................Sunscreen
Octocrylene 7%...........................................................Sunscreen

Uses

- helps prevent sunburn

- if used as directed with other sunprotection measures (see Directions), decreases the risk of skin cancer and early skin aging caused by the sun

Keep out of reach of children. If swallowed, get medical help
or contact a Poison Control Center right away.

Stop use and ask a doctor if rash occurs

Warnings
For external use only
Do not use on damaged or broken skin
When using this product keep out of eyes. Rinse with water
to remove.

Directions

- apply liberally 15 minutes before sun exposure

- use a water resistant sunscreen if swimming or sweating

- reapply at least every 2 hours
- children under 6 months: Ask a doctor
- Sun Protection Measures.Spending time in the sun increases your risk of skin cancer and early skin aging. To decrease this risk, regularly use a sunscreen with a Broad Spectrum SPF value of 15 or higher and other sun protection measures including:

- limit time in the sun, especially from 10 a.m. - 2 p.m.

- wear long-sleeve shirts, pants, hats, and sunglasses

Inactive ingredients
Acrylates/C10-30 Alkyl AcrylateCrosspolymer, Acrylates/Dimethicone Copolymer, Actinidia Chinensis(Kiwi) Fruit Water, Alcohol,Allantoin, Aluminum Starch Octenylsuccinate, Arachidy lAlcohol, Arachidyl Glucoside, Arginine, Behenyl Alcohol, Benzyl Alcohol, Bisabolol, Butylene Glycol, Butyrospermum Parkii(Shea) Butter, Chlorphenesin, Cocos Nucifera Fruit Extract, Cyclopentasiloxane, Dipropylene Glycol, Disodium EDTA, Ethylhexylglycerin,Fragrance/Parfum, Glycerin,Glyceryl Stearate, Hydrogenated Lecithin, Lauroyl Lysine, Lecithin,Maltodextrin, Moringa Oleifera Leaf Extract, PEG-100 Stearate, Phenethyl Alcohol, Polygonum Aviculare Extract, Royal Jelly,Sodium Ascorbyl Phosphate,Sophora Flavescens Root Extract, Styrene/Acrylates Copolymer, Tetrapeptide-45,Water/Aqua

PACKAGE LABEL

Jafra Royal

Royal Jelly

Revitalize

1 Gentle Cleansing Milk
30 ml 1 FL OZ (US)
1 Longevity Crème
14 ml 0.47 FL OZ (US)
1 Spot Serum
7,5 ml .25 FL OZ (US)
1 Solar Protection Fluid Broad Spectrum SPF 50
14 ml 0.47 FL OZ (US)
Contains: 4 Sample
Total Content 65,5 ml 2.21 FL OZ (US)